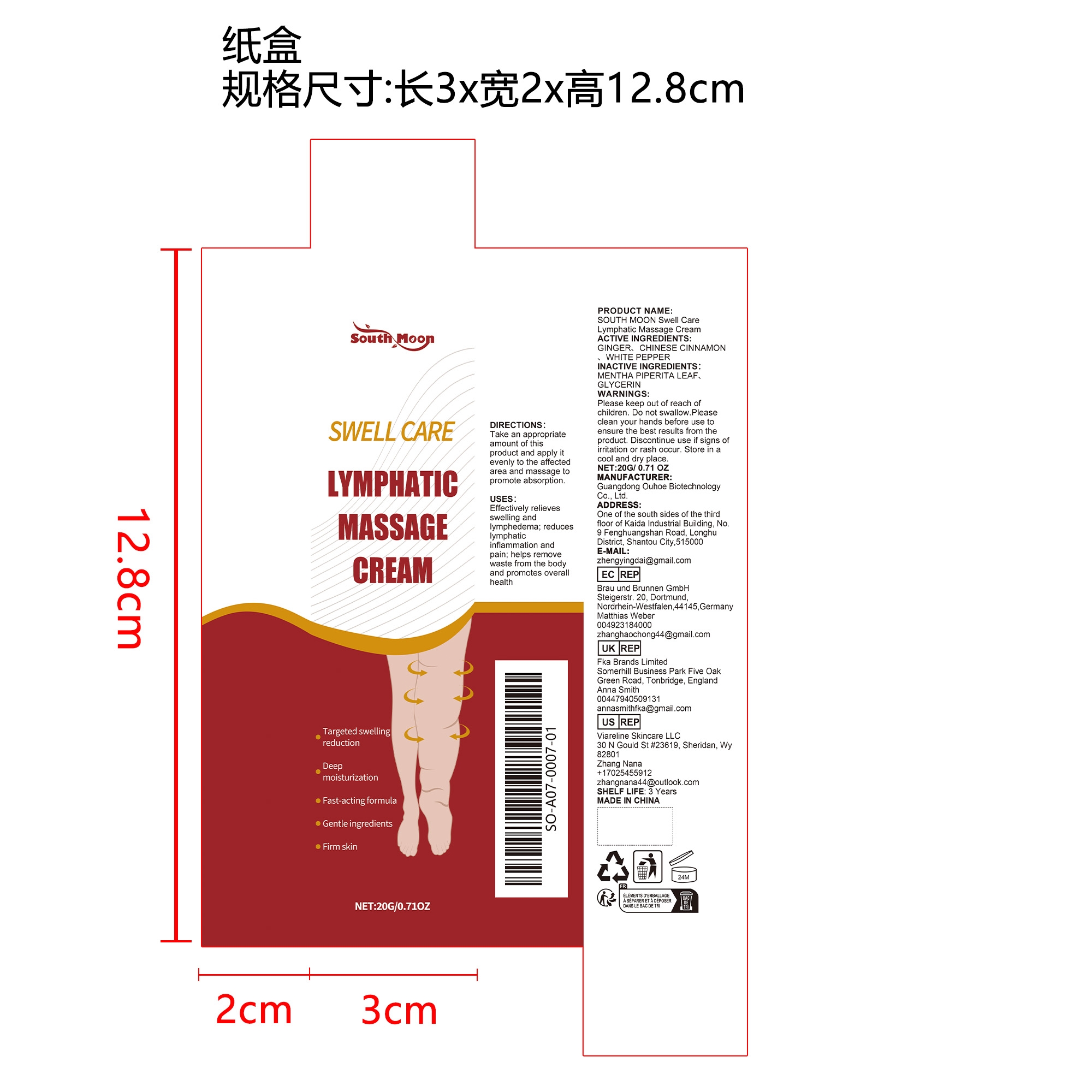 DRUG LABEL: SOUTH MOON Swell Care Lymphatic Massage Cream
NDC: 84744-064 | Form: CREAM
Manufacturer: Guangdong Ouhoe Biotechnology Co., Ltd.
Category: otc | Type: HUMAN OTC DRUG LABEL
Date: 20241024

ACTIVE INGREDIENTS: WHITE PEPPER 3 g/20 g; CHINESE CINNAMON 2 g/20 g; GINGER 6 g/20 g
INACTIVE INGREDIENTS: GLYCERIN 6 g/20 g; MENTHA PIPERITA LEAF 3 g/20 g

ACTIVE INGREDIENTS

GINGER、CHINESE CINNAMON 、WHITE PEPPER

PURPOSE

Effectively relieves swelling and lymphedema; reduces lymphatic inflammation and pain; helps remove waste from the body and promotes overall health

USE

Take an appropriate amount of thisproduct and apply it evenly to the affected area and massage to promote absorption.

WARNINGS

Please keep out of reach of children. Do not swallow.Please clean your hands before use to ensure the best results from the product. Discontinue use if signs of irritation or rash occur. Store in a cool and dry place.

KEEP OUT OF REACH OF CHILDREN

Please keep out of reach of children. Do not swallow.

STOP USE

Discontinue use if signs of irritation or rash occur.

DO NOT USE

Discontinue use if signs of irritation or rash occur.

STORAGE AND HANDLING

Store in a cool and dry place.

INACTIVE INGREDIENT

MENTHA PIPERITA LEAF、GLYCERIN